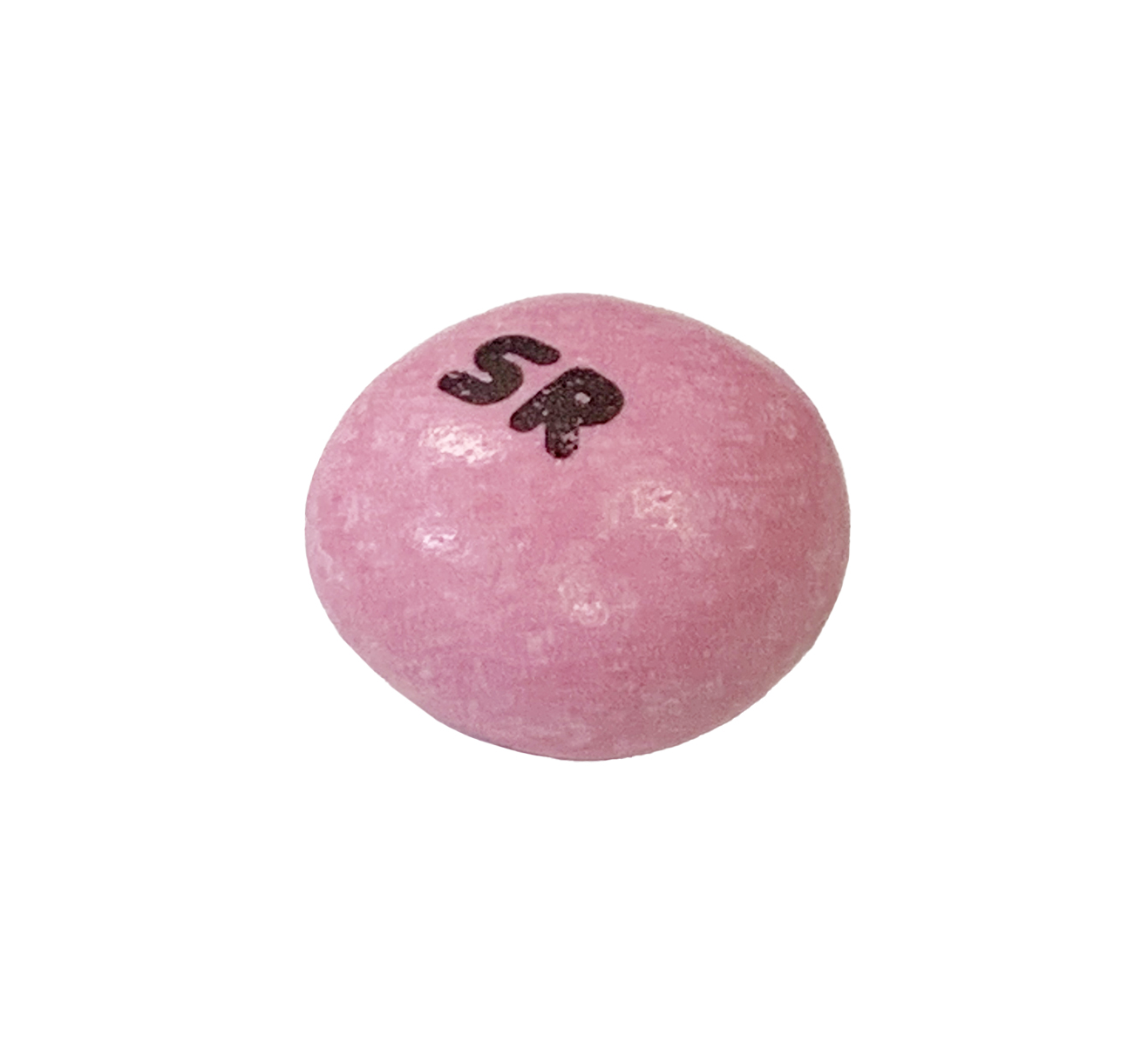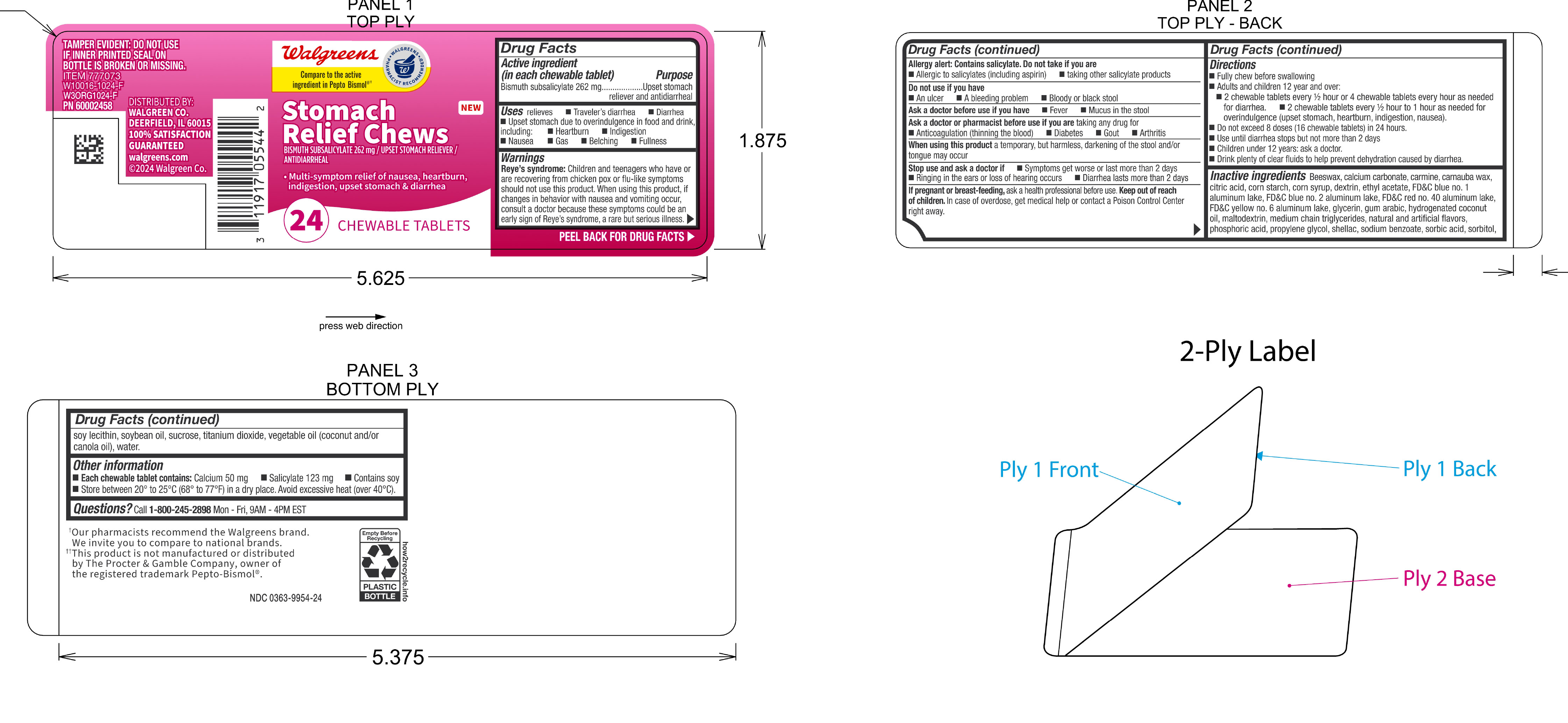 DRUG LABEL: Walgreens Bismuth Stomach Relief
NDC: 0363-9954 | Form: TABLET, CHEWABLE
Manufacturer: Walgreens
Category: otc | Type: HUMAN OTC DRUG LABEL
Date: 20251223

ACTIVE INGREDIENTS: BISMUTH SUBSALICYLATE 262 mg/1 1
INACTIVE INGREDIENTS: WATER

Bismuth subsalicylate 262 mg

Active ingredient (in each chewable tablet)

Bismuth subsalicylate 262 mg

Purpose

Upset stomach reliever and antidiarrheal

INDICATIONS AND USAGE

Uses relieves

- Traveler's diarrhea
- Diarrhea
- Upset stomach due to overindulgence in food or drink, including:
- Heartburn
- Indigestion
- Nausea
- Gas
- Belching
- Fullness

Warnings

Reye's syndrome: Children and teenagers who have or are recovering from chicken pox or flu-like symptoms should not use this product. When using this product, if changes in behavior with nausea and vomiting occur, consult a doctor because these symptoms could be an early sign of Reye's syndrome, a rare but serious illness.

Allergy alert: Contains salicylate. Do not take if you are

- Allergic to salicylates (including aspirin)
- taking other salicylate products

Do not use if you have

- An ulcer
- A bleeding problem
- Bloody or black stool

Ask a doctor before use if you have

- Fever
- Mucus in the stool

Ask a doctor or pharmacist before use if you are taking any drug for

- Anticoagulation (thinning the blood)
- Diabetes
- Gout
- Arthritis

When using this product a temporary, but harmless, darkening of the stool and/or tongue may occur

Stop use and ask doctor if

- Symptoms get worse or last more than 2 days
- Ringing in the ears or loss of hearing occurs
- Diarrhea lasts more than 2 days

PREGNANCY OR BREAST FEEDING

If pregnant or breast-feeding, ask a health professional before use.

Keep out of reach of children.

OVERDOSAGE

In case of overdose, get medical help or contact a Poison Control Center right away.

Directions

- Fully chew before swallowing
- Adults and children 12 years and over:
- 2 chewable tablets every 1/2 hour or 4 chewable tablets every hour as needed for diarrhea
- 2 chewable tablets every 1/2 hour to 1 hour as needed for overindulgence (upset stomach, heartburn, indigestion, nausea).
- Do not exceed 8 doses (15 chewable tablets) in 24 hours
- Use until diarrhea stops but not more than 2 days
- Children under 12 years: ask a doctor
- Drink plenty of clear fluids to help prevent dehydration caused by diarrhea.

INACTIVE INGREDIENT

Inactive ingredients: Beeswax, calcium carbonate, carmine, carnauba wax, citric acid, corn starch, corn syrup, dextrin, ethyl acetate, FD&C blue no. 1 aluminum lake, FD&C blue no. 2 aluminum lake, FD&C red no. 40 aluminum lake, FD&C yellow no. 6 aluminum lake, glycerin, gum arabic, hydrogenated coconut oil, maltodextrin, natural and artificial flavors, phosphoric acid, propylene glycol, shellac, sodium benzoate, sorbic acid, sorbitol, soy lecithin, sucrose, titanium dioxide, vegetable oil (coconut and/or canola oil), water.

Other information

- Each chewable tablet contains: Calcium 50 mg
- Salicylate 123 mg
- Low sodium
- Store at no greater then 25°C (77°F).
- Avoid excessive heat (over 40°C).

QUESTIONS

Questions? Call 1-800-245-2898 Monday - Friday, 9AM - 4PM EST